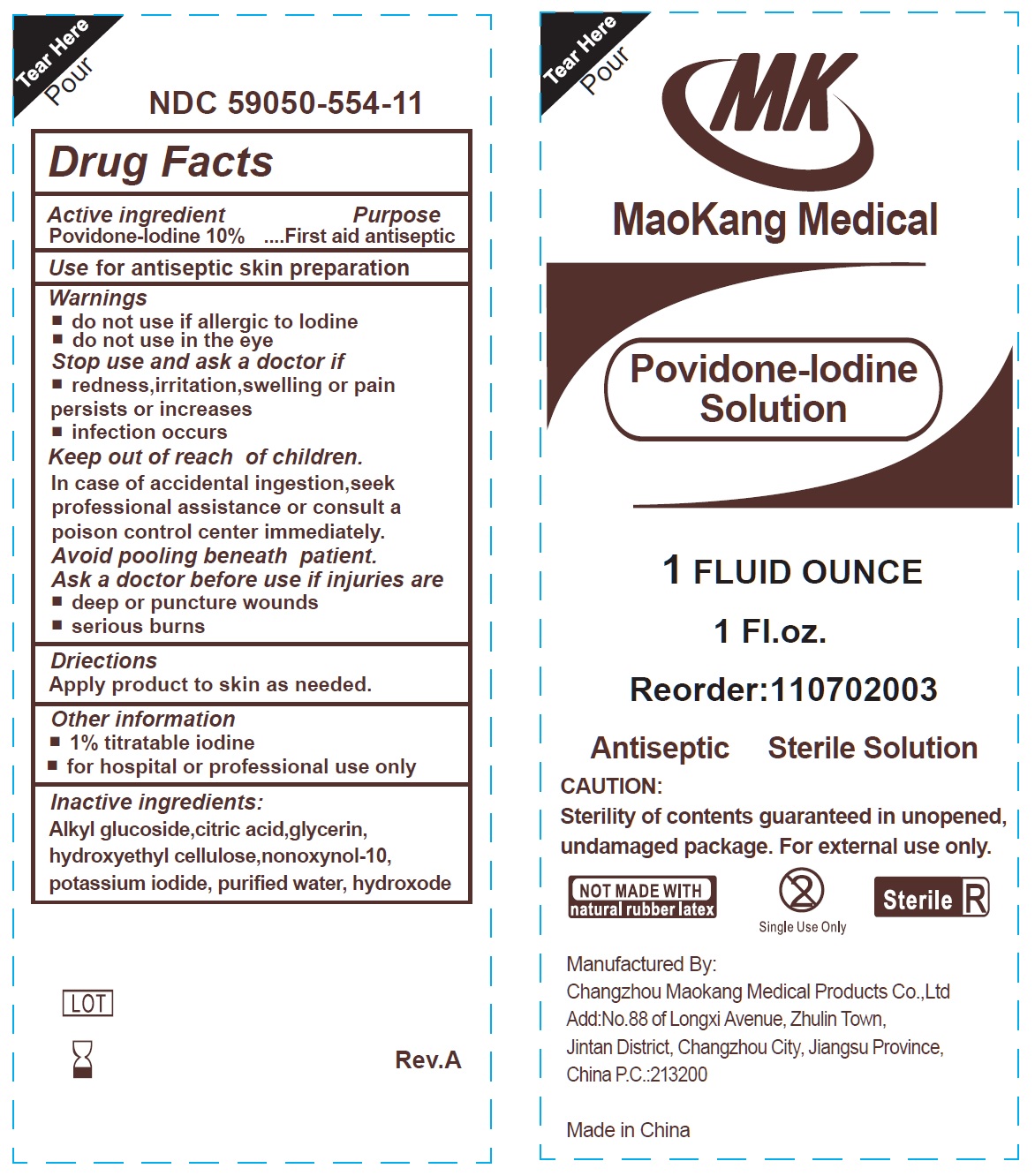 DRUG LABEL: Povidone-Iodine Solution Sterile
NDC: 59050-554 | Form: LIQUID
Manufacturer: Changzhou Maokang Medical Products Co., Ltd
Category: otc | Type: HUMAN OTC DRUG LABEL
Date: 20241121

ACTIVE INGREDIENTS: POVIDONE-IODINE 100 mg/1 mL
INACTIVE INGREDIENTS: CITRIC ACID MONOHYDRATE; GLYCERIN; HYDROXYETHYL CELLULOSE, UNSPECIFIED; NONOXYNOL-10; POTASSIUM IODIDE; WATER

Povidone-Iodine Solution Sterile

Active ingredient

Povidone-Iodine 10%

Purpose

First aid antiseptic

Use

for antiseptic skin preparation

Warnings

do not use

- if allergic to Iodine
- do not use in the eye

Stop use and ask a doctor if

- redness, irritation, swelling or pain persists or increases
- infection occurs

Keep out of reavh of children.

In case of accidental ingestion, seek professional assistance or consult a poison control center immediately.

Avoid pooling beneath patient.

Ask a doctor before use if injuries are

- deep or punture wounds
- serious burns

Directions

Apply product to skin as needed.

Other information

- 1% titratable iodine
- for hospital or professional use only

Inactive ingredients:

Alkyl glucoside,citric acid,glycerin, hydroxyethyl cellulose,nonoxynol-10, potassium iodide, purified water, hydroxode